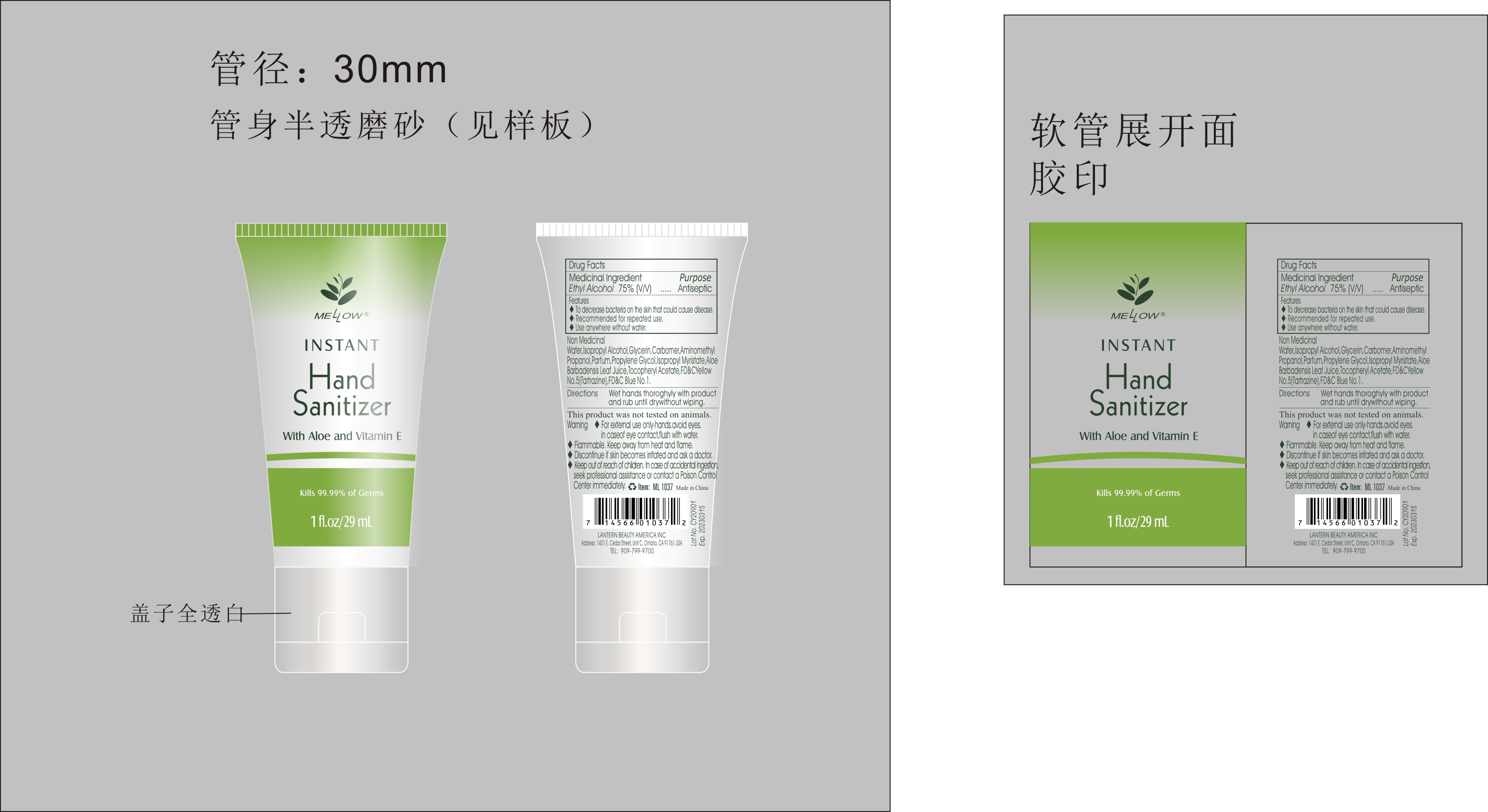 DRUG LABEL: Mellow hand sanitizer with aloe and vitamin E 29mL
NDC: 54860-398 | Form: GEL
Manufacturer: Shenzhen Lantern Scicence Co Ltd
Category: otc | Type: HUMAN OTC DRUG LABEL
Date: 20220803

ACTIVE INGREDIENTS: ALCOHOL 75 mL/100 mL
INACTIVE INGREDIENTS: ALOE VERA LEAF 0.1 mL/100 mL; PIGMENT BLUE 1 0.000008 mL/100 mL; PROPYLENE GLYCOL 0.1 mL/100 mL; ISOPROPYL MYRISTATE 0.001 mL/100 mL; ISOPROPYL ALCOHOL 0.5 mL/100 mL; .ALPHA.-TOCOPHEROL ACETATE 0.001 mL/100 mL; ALOE 0.2 mL/100 mL; AMINOMETHYLPROPANOL 0.14 mL/100 mL; WATER 23.457972 mL/100 mL; GLYCERIN 0.5 mL/100 mL; BASIC YELLOW 5 0.00002 mL/100 mL

Mellow hand sanitizer with aloe and vitamin E 29mL

Medicical Ingredient

Medicical Ingredient Purpose

Ethyl Alcohol 75%（V/V） Antiseptic

Features

To decrease bacteria on the skin that could cause disease.

DOSAGE AND ADMINISTRATION

Recommended for repeated use.

use anywhere without water.

Warning

For external use only-hands.avoid eyes,in case of eye contact,flush with water

Flammable,keep away from heat and flame.

Discontinue if skin becomes irritated and ask a doctor.

Keep out of reach of children.In case of accidental ingestion.

seek professional assistance or contact a Poison Control.

WARNINGS AND PRECAUTIONS

For external use only.

Flammable, keep away from heat and flame.

STOP USE

Discontinue if skin becomes irritated and ask a doctor .

Keep out of reach of children. In case of accidental ingestion, seek professional assistance or contact a poson control center immediately.

Non-Medicinal

Alcohol，Aqua(water)，Isopropyl Alcohol，Glycerin，Carbomer，Aminomethyl Propanol，Parfum，Propylene Glycol，ISOPROPYL MYRISTATE，ALOE BARBADENSIS LEAF JUICE，Tocopheryl Acetate，YELLOW 5，BLUE 1.

Directions

Wet hands thoroughly with product and rub until dry without wiping

For children under 6, use only under adult supervision.

Not recommended for infants.

When using this product

keep out of eyes. In case of contact with eyes, flush thoroughly with water.

Do not inhale or ingest.

Avoid contact with broken skin.

Other information

Do not store above 105F.

May discolor some fabrics.

Harmful to wood finishes and plastics.